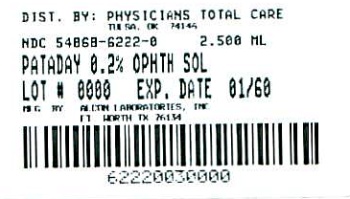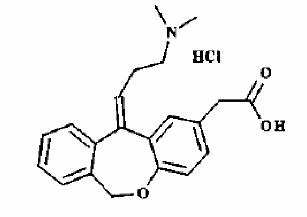 DRUG LABEL: Pataday
NDC: 54868-6222 | Form: SOLUTION/ DROPS
Manufacturer: Physicians Total Care, Inc.
Category: prescription | Type: HUMAN PRESCRIPTION DRUG LABEL
Date: 20110105

ACTIVE INGREDIENTS: OLOPATADINE HYDROCHLORIDE 2 mg/1 mL
INACTIVE INGREDIENTS: POVIDONE; SODIUM PHOSPHATE, DIBASIC; SODIUM CHLORIDE; EDETATE DISODIUM; BENZALKONIUM CHLORIDE 0.1 mg/1 mL; HYDROCHLORIC ACID; SODIUM HYDROXIDE; WATER

DESCRIPTION

PATADAY™ (olopatadine hydrochloride ophthalmic solution) 0.2% is a sterile ophthalmic solution containing olopatadine for topical administration to the eyes.

Olopatadine hydrochloride is a white, crystalline, water-soluble powder with a molecular weight of 373.88 and a molecular formula of C21H23NO3· HCl. The chemical structure is presented below:

Chemical Name: 11-[(Z)-3-(Dimethylamino) propylidene]-6-11-dihydrodibenz[b,e] oxepin-2-acetic acid, hydrochloride

Each mL of PATADAY™ solution contains: Active: 2.22 mg olopatadine hydrochloride equivalent to 2 mg olopatadine. Inactives: povidone; dibasic sodium phosphate; sodium chloride; edetate disodium; benzalkonium chloride 0.01% (preservative) hydrochloric acid / sodium hydroxide (adjust pH); and purified water.

It has a pH of approximately 7 and an osmolality of approximately 300 mOsm/kg.

CLINICAL PHARMACOLOGY

Olopatadine is a relatively selective histamine H1 antagonist and an inhibitor of the release of histamine from the mast cells. Decreased chemotaxis and inhibition of eosinophil activation has also been demonstrated. Olopatadine is devoid of effects on alpha-adrenergic, dopaminergic, and muscarinic type 1 and 2 receptors.

Systemic bioavailability data upon topical ocular administration of PATADAY™ solution are not available. Following topical ocular administration of olopatadine 0.15% ophthalmic solution in man, olopatadine was shown to have a low systemic exposure. Two studies in normal volunteers (totaling 24 subjects) dosed bilaterally with olopatadine 0.15% ophthalmic solution once every 12 hours for 2 weeks demonstrated plasma concentrations to be generally below the quantitation limit of the assay (< 0.5 ng/mL). Samples in which olopatadine was quantifiable were typically found within 2 hours of dosing and ranged from 0.5 to 1.3 ng/mL. The elimination half-life in plasma following oral dosing was 8 to 12 hours, and elimination was predominantly through renal excretion. Approximately 60 - 70% of the dose was recovered in the urine as parent drug. Two metabolites, the mono-desmethyl and the N-oxide, were detected at low concentrations in the urine.

CLINICAL STUDIES

Results from clinical studies of up to 12 weeks duration demonstrate that PATADAY™ solution when dosed once a day is effective in the treatment of ocular itching associated with allergic conjunctivitis.

INDICATIONS AND USAGE

PATADAY™solution is indicated for the treatment of ocular itching associated with allergic conjunctivitis.

CONTRAINDICATIONS

Hypersensitivity to any components of this product.

WARNINGS

For topical ocular use only. Not for injection or oral use.

PRECAUTIONS

Information for Patients

As with any eye drop, to prevent contaminating the dropper tip and solution, care should be taken not to touch the eyelids or surrounding areas with the dropper tip of the bottle. Keep bottle tightly closed when not in use. Patients should be advised not to wear a contact lens if their eye is red.

PATADAY™ (olopatadine hydrochloride ophthalmic solution) 0.2% should not be used to treat contact lens related irritation. The preservative in PATADAY™ solution, benzalkonium chloride, may be absorbed by soft contact lenses. Patients who wear soft contact lenses and whose eyes are not red, should be instructed to wait at least ten minutes after instilling PATADAY™ (olopatadine hydrochloride ophthalmic solution) 0.2% before they insert their contact lenses.

Carcinogenesis, Mutagenesis, Impairment of Fertility

Olopatadine administered orally was not carcinogenic in mice and rats in doses up to 500 mg/kg/day and 200 mg/kg/day, respectively. Based on a 40 µL drop size and a 50 kg person, these doses were approximately 150,000 and 50,000 times higher than the maximum recommended ocular human dose (MROHD). No mutagenic potential was observed when olopatadine was tested in an in vitro bacterial reverse mutation (Ames) test, an in vitro mammalian chromosome aberration assay or an in vivo mouse micronucleus test. Olopatadine administered to male and female rats at oral doses of approximately 100,000 times MROHD level resulted in a slight decrease in the fertility index and reduced implantation rate; no effects on reproductive function were observed at doses of approximately 15,000 times the MROHD level.

Pregnancy Teratogenic effects: Pregnancy Category C

Olopatadine was found not to be teratogenic in rats and rabbits. However, rats treated at 600 mg/kg/day, or 150,000 times the MROHD and rabbits treated at 400 mg/kg/day, or approximately 100,000 times the MROHD, during organogenesis showed a decrease in live fetuses. In addition, rats treated with 600 mg/kg/day of olopatadine during organogenesis showed a decrease in fetal weight. Further, rats treated with 600 mg/kg/day of olopatadine during late gestation through the lactation period showed a decrease in neonatal survival and body weight.

There are, however, no adequate and well-controlled studies in pregnant women. Because animal studies are not always predictive of human responses, this drug should be used in pregnant women only if the potential benefit to the mother justifies the potential risk to the embryo or fetus.

Nursing Mothers

Olopatadine has been identified in the milk of nursing rats following oral administration. It is not known whether topical ocular administration could result in sufficient systemic absorption to produce detectable quantities in the human breast milk. Nevertheless, caution should be exercised when PATADAY™ (olopatadine hydrochloride ophthalmic solution) 0.2% is administered to a nursing mother.

Pediatric Use

Safety and effectiveness in pediatric patients below the age of 3 years have not been established.

Geriatric Use

No overall differences in safety and effectiveness have been observed between elderly and younger patients.

ADVERSE REACTIONS

Symptoms similar to cold syndrome and pharyngitis were reported at an incidence of approximately 10%.

The following adverse experiences have been reported in 5% or less of patients:

Ocular: blurred vision, burning or stinging, conjunctivitis, dry eye, foreign body sensation, hyperemia, hypersensitivity, keratitis, lid edema, pain and ocular pruritus.

Non-ocular: asthenia, back pain, flu syndrome, headache, increased cough, infection, nausea, rhinitis, sinusitis and taste perversion.

Some of these events were similar to the underlying disease being studied.

DOSAGE AND ADMINISTRATION

The recommended dose is one drop in each affected eye once a day.

HOW SUPPLIED

PATADAY™(olopatadine hydrochloride ophthalmic solution) 0.2% is supplied in a white, oval, low density polyethylene DROP-TAINER® dispenser with a natural low density polyethylene dispensing plug and a white polypropylene cap. Tamper evidence is provided with a shrink band around the closure and neck area of the package.

NDC 54868-6222-0 2.5 mL fill in 4 mL oval bottle

Storage

Store at 2oC to 25oC (36oF to 77oF)

U.S. Patents Nos. 4,871,865; 4,923,892; 5,116,863; 5,641,805; 6,995,186

Rx Only

© 2006 Alcon, Inc.

Relabeling of "Additional" barcode label by:
Physicians Total Care, Inc.
Tulsa, OK 74146

PRINCIPAL DISPLAY PANEL

PATADAY™(olopatadine hydrochloride ophthalmic solution) 0.2%

2.5 mL